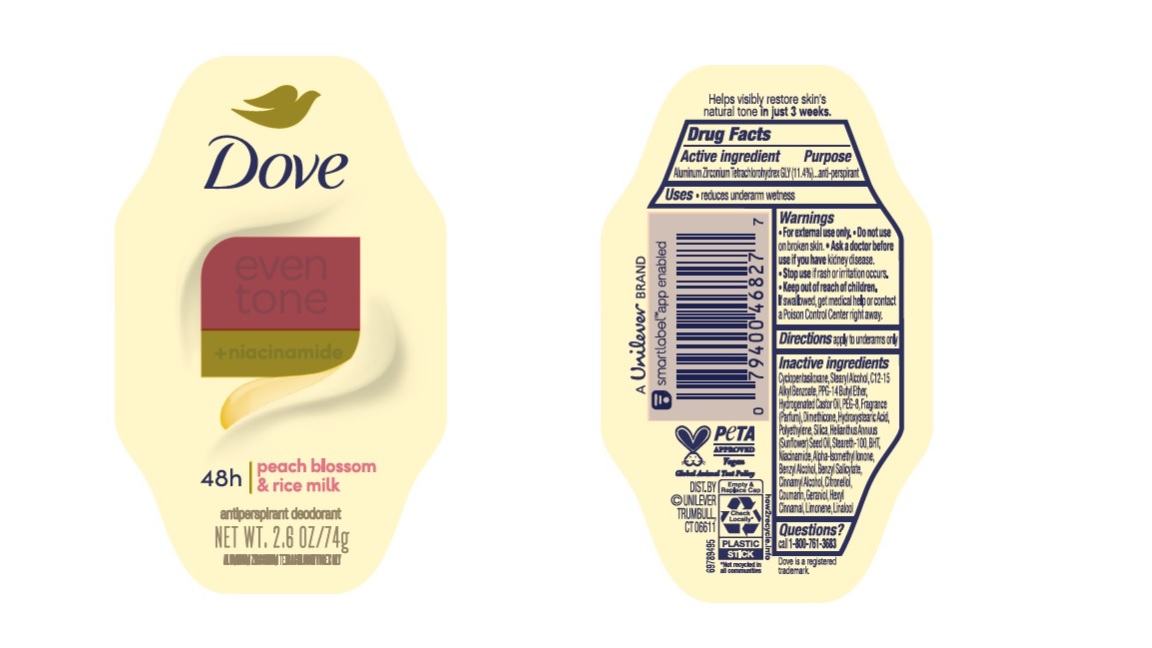 DRUG LABEL: Dove
NDC: 64942-2135 | Form: STICK
Manufacturer: Conopco Inc. d/b/a/ Unilever
Category: otc | Type: HUMAN OTC DRUG LABEL
Date: 20241106

ACTIVE INGREDIENTS: ALUMINUM ZIRCONIUM TETRACHLOROHYDREX GLY 11.4 g/100 g
INACTIVE INGREDIENTS: STEARYL ALCOHOL; HYDROGENATED CASTOR OIL; HIGH DENSITY POLYETHYLENE; CYCLOMETHICONE 5; BUTYLATED HYDROXYTOLUENE; PPG-14 BUTYL ETHER; SUNFLOWER OIL; SILICON DIOXIDE; ALKYL (C12-15) BENZOATE; DIMETHICONE; STEARETH-100; POLYETHYLENE GLYCOL 400; NIACINAMIDE; BENZYL ALCOHOL; CINNAMYL ALCOHOL; .BETA.-CITRONELLOL, (R)-; LIMONENE, (+)-; 12-HYDROXYSTEARIC ACID; LINALOOL, (+/-)-; BENZYL SALICYLATE; COUMARIN; GERANIOL; .ALPHA.-HEXYLCINNAMALDEHYDE

Dove Even Tone+ Niacinamide Peach Blossom & Rice Milk Antiperspirant Deodorant

Drug Facts

Active ingredient

Aluminum Zirconium Tetrachlorohydrex GLY (11.4 %)

Purpose

antiperspirant

Uses

• reduces underarm wetness

Warnings

• For external use only.
• Do not use on broken skin .
• Ask a doctor before use if you have kidney disease.
• Stop use if rash or irritation occurs.

• Keep out of reach of children.

If swallowed, get medical help or contact a Poison Control Center right away.

Directions

apply to underarms only

Inactive ingredients

Cyclopentasiloxane, Stearyl Alcohol, C12-15 Alkyl Benzoate, PPG-14 Butyl Ether, Hydrogenated Castor Oil, PEG-8, Fragrance (Parfum), Dimethicone, Hydroxystearic Acid, Polyethylene, Silica, Helianthus Annuus (Sunflower) Seed Oil, Steareth-100, BHT, Niacinamide, Benzyl Alcohol, Benzyl Salicylate, Citronellol, Coumarin, Geraniol. Hexyl Cinnamal, Limonene, Linalool.

Questions?

Call 1-800-761-3683